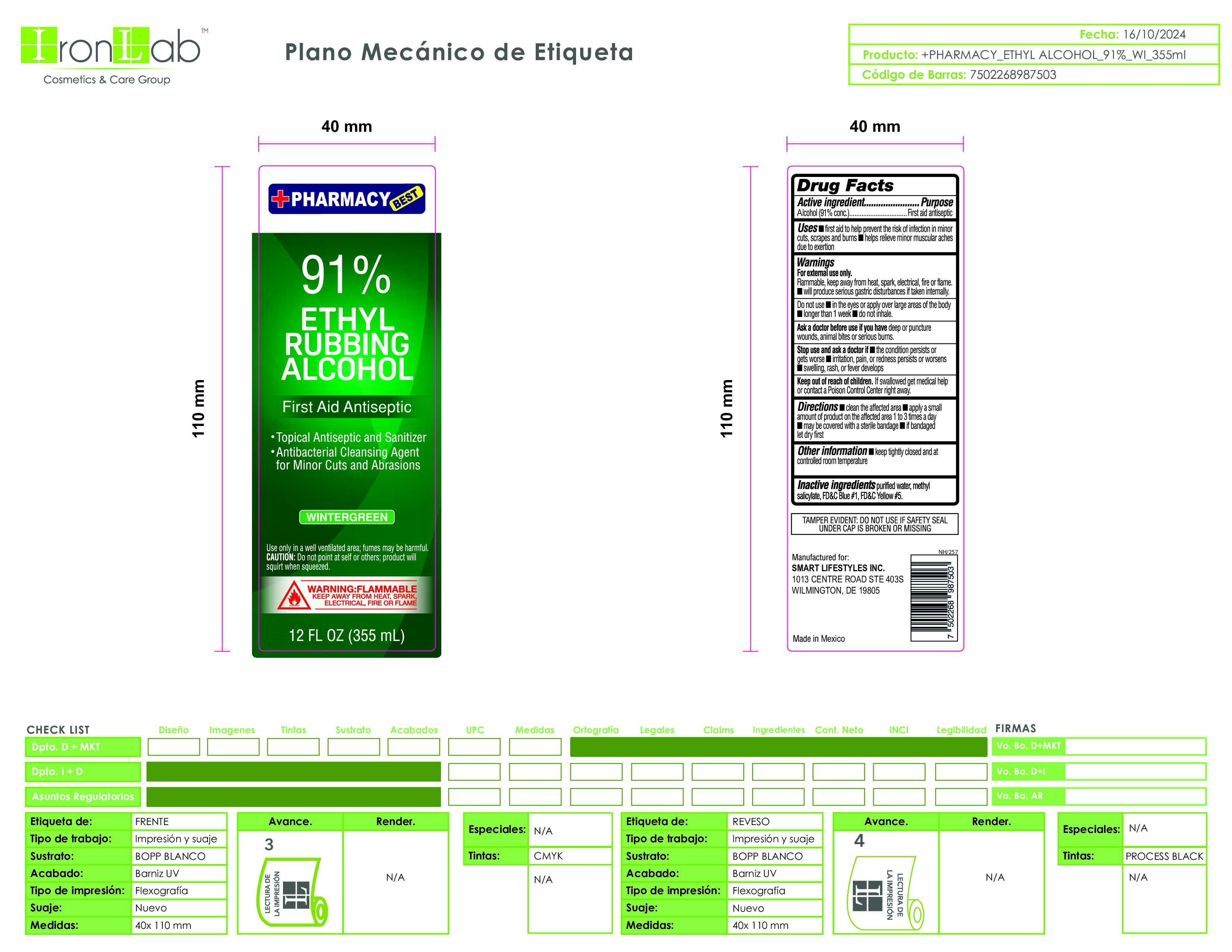 DRUG LABEL: Wintergreen 91 - Iron Lab
NDC: 74375-010 | Form: LIQUID
Manufacturer: Iron Lab SA de CV
Category: otc | Type: HUMAN OTC DRUG LABEL
Date: 20260217

ACTIVE INGREDIENTS: ALCOHOL 91 mL/100 mL
INACTIVE INGREDIENTS: WATER; FD&C BLUE NO. 1; METHYL SALICYLATE; FD&C YELLOW NO. 5

Winter Green 91 Sanitizer Iron Lab

DOSAGE AND ADMINISTRATION

Thoroughly cover your hands with product and allow to dry without wiping. Children under 6 years of age should be supervised when using this product. Not recommended for infants.

ACTIVE INGREDIENT

Ethyl Alcohol 91%

INACTIVE INGREDIENT

purified water, methyl salicylate, FD&C Blue #1, FD&C Yellow #5

PURPOSE

Antiseptic Alcohol

WARNINGS

For external use only: hands. Flammable, Keep away from fire of flame.

OTHER SAFETY INFORMATION

Store below 105°F. May discolor some fabrics. Harmful to wood finishes and plastic

KEEP OUT OF REACH OF CHILDREN

If swallowed get medical helo or contact a Poison Control Center right away.

STOP USE

the condition persists or gets worse irritation, pain, or redness persists or worsens i swelling, rash, or fever develops

Do Not Use int he eyes or apply over large areas of the body

Longer Than 1 week

Do Not Inhale

INDICATIONS AND USAGE

first aid to help prevent the risk of infection in minor cuts, scrapes and burns helps relieve minor muscular aches due to exertion

PACKAGE LABEL

Winter Green 91